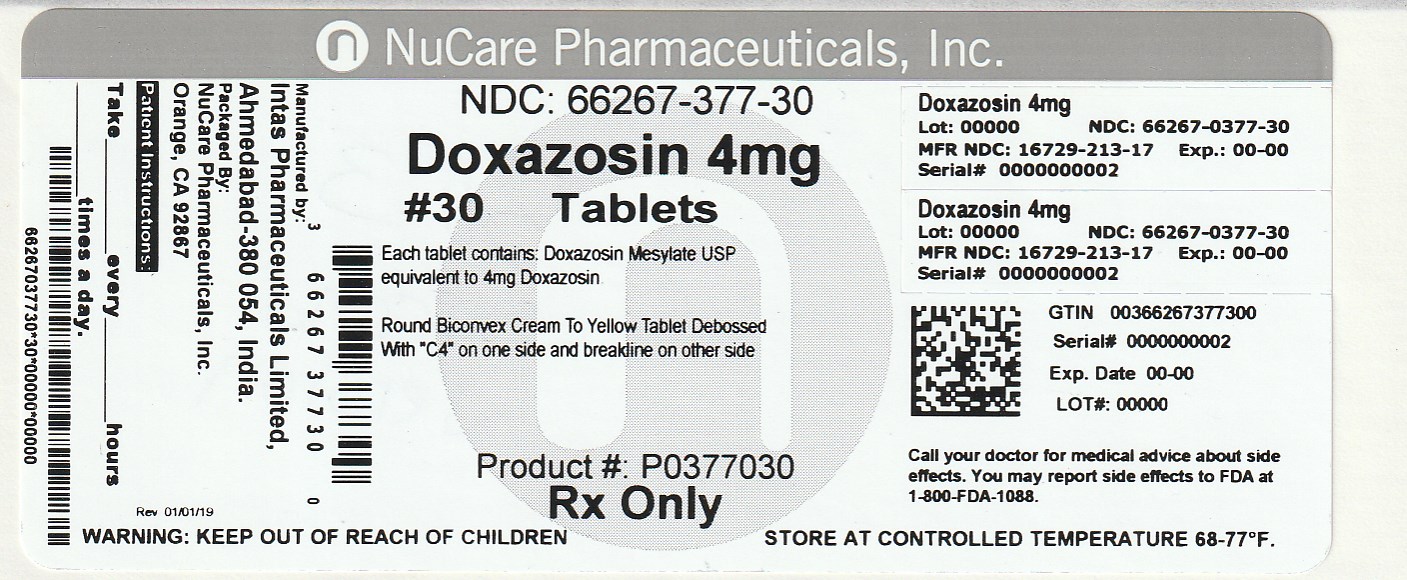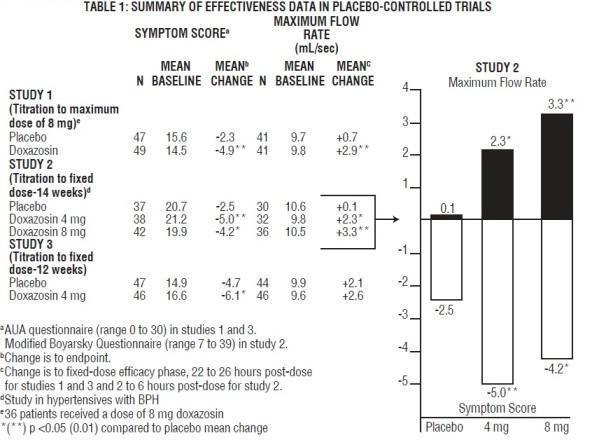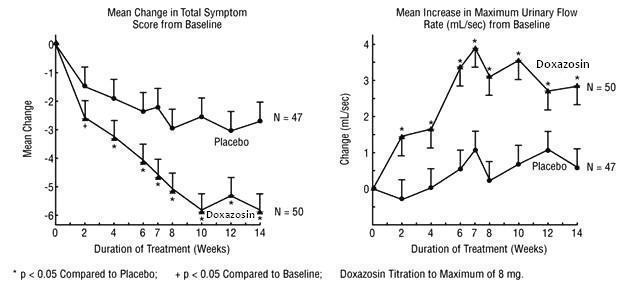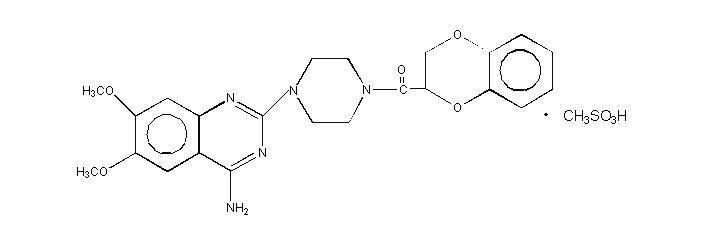 DRUG LABEL: Doxazosin
NDC: 66267-377 | Form: TABLET
Manufacturer: NuCare Pharmaceuticals, Inc.
Category: prescription | Type: HUMAN PRESCRIPTION DRUG LABEL
Date: 20240814

ACTIVE INGREDIENTS: DOXAZOSIN MESYLATE 4 mg/1 1
INACTIVE INGREDIENTS: CELLULOSE, MICROCRYSTALLINE; LACTOSE MONOHYDRATE; SODIUM STARCH GLYCOLATE TYPE A POTATO; SODIUM LAURYL SULFATE; FERRIC OXIDE YELLOW

Doxazosin Tablets USP

DESCRIPTION

Doxazosin mesylate is a quinazoline compound that is a selective inhibitor of the alpha1 subtype of alpha-adrenergic receptors. The chemical name of doxazosin mesylate is 1-(4-amino-6,7-dimethoxy-2-quinazolinyl)-4-(1,4-benzodioxan-2-ylcarbonyl) piperazine methanesulfonate. The empirical formula for doxazosin mesylate is C23H25N5O5 • CH4O3S and the molecular weight is 547.6. It has the following structure:

Doxazosin mesylate is freely soluble in dimethylsulfoxide, soluble in dimethylformamide, slightly soluble in methanol, ethanol, and water (0.8% at 25°C), and very slightly soluble in acetone and methylene chloride. Doxazosin tablets USP are available as colored tablets for oral use and contains 1 mg (White to off white), 2 mg (Cream to yellow), 4 mg (Cream to yellow) and 8 mg (White to off white) of doxazosin as the free base.

The inactive ingredients for all tablets are: lactose monohydrate, microcrystalline cellulose, sodium lauryl sulfate, magnesium stearate and sodium starch glycolate. The 2 mg & 4 mg tablet contains ferric oxide yellow.

CLINICAL PHARMACOLOGY

Pharmacodynamics

A. Benign Prostatic Hyperplasia (BPH)

Benign prostatic hyperplasia (BPH) is a common cause of urinary outflow obstruction in aging males. Severe BPH may lead to urinary retention and renal damage. A static and a dynamic component contribute to the symptoms and reduced urinary flow rate associated with BPH. The static component is related to an increase in prostate size caused, in part, by a proliferation of smooth muscle cells in the prostatic stroma. However, the severity of BPH symptoms and the degree of urethral obstruction do not correlate well with the size of the prostate. The dynamic component of BPH is associated with an increase in smooth muscle tone in the prostate and bladder neck. The degree of tone in this area is mediated by the alpha1 adrenoceptor, which is present in high density in the prostatic stroma, prostatic capsule and bladder neck. Blockade of the alpha1 receptor decreases urethral resistance and may relieve the obstruction and BPH symptoms. In the human prostate, doxazosin antagonizes phenylephrine (alpha1 agonist)-induced contractions, in vitro, and binds with high affinity to the alpha1c adrenoceptor. The receptor subtype is thought to be the predominant functional type in the prostate. Doxazosin acts within 1 to 2 weeks to decrease the severity of BPH symptoms and improve urinary flow rate. Since alpha1 adrenoceptors are of low density in the urinary bladder (apart from the bladder neck), doxazosin should maintain bladder contractility.

The efficacy of doxazosin was evaluated extensively in over 900 patients with BPH in double-blind, placebo-controlled trials. Doxazosin treatment was superior to placebo in improving patient symptoms and urinary flow rate. Significant relief with doxazosin was seen as early as one week into the treatment regimen, with doxazosin-treated patients (N=173) showing a significant (p<0.01) increase in maximum flow rate of 0.8 mL/sec compared to a decrease of 0.5 mL/sec in the placebo group (N=41). In long-term studies, improvement was maintained for up to 2 years of treatment. In 66 to 71% of patients, improvements above baseline were seen in both symptoms and maximum urinary flow rate.

In three placebo-controlled studies of 14 to 16 weeks' duration, obstructive symptoms (hesitation, intermittency, dribbling, weak urinary stream, incomplete emptying of the bladder) and irritative symptoms (nocturia, daytime frequency, urgency, burning) of BPH were evaluated at each visit by patient-assessed symptom questionnaires. The bothersomeness of symptoms was measured with a modified Boyarsky questionnaire. Symptom severity/frequency was assessed using a modified Boyarsky questionnaire or an AUA-based questionnaire. Uroflowmetric evaluations were performed at times of peak (2 to 6 hours post-dose) and/or trough (24 hours post-dose) plasma concentrations of doxazosin.

The results from the three placebo-controlled studies (N=609) showing significant efficacy with 4 mg and 8 mg doxazosin are summarized in Table 1. In all three studies, doxazosin resulted in statistically significant relief of obstructive and irritative symptoms compared to placebo. Statistically significant improvements of 2.3 to 3.3 mL/sec in maximum flow rate were seen with doxazosin in Studies 1 and 2, compared to 0.1 to 0.7 mL/sec with placebo.

In one fixed-dose study (Study 2), doxazosin therapy (4 to 8 mg, once daily) resulted in a significant and sustained improvement in maximum urinary flow rate of 2.3 to 3.3 mL/sec (Table 1) compared to placebo (0.1 mL/sec). In this study, the only study in which weekly evaluations were made, significant improvement with doxazosin vs. placebo was seen after one week. The proportion of patients who responded with a maximum flow rate improvement of ≥3 mL/sec was significantly larger with doxazosin (34 to 42%) than placebo (13 to 17%). A significantly greater improvement was also seen in average flow rate with doxazosin (1.6 mL/sec) than with placebo (0.2 mL/sec). The onset and time course of symptom relief and increased urinary flow from Study 1 are illustrated in Figure 1.

Figure 1 – Study 1

In BPH patients (N=450) treated for up to 2 years in open-label studies, doxazosin therapy resulted in significant improvement above baseline in urinary flow rates and BPH symptoms. The significant effects of doxazosin were maintained over the entire treatment period.

Although blockade of alpha1 adrenoceptors also lowers blood pressure in hypertensive patients with increased peripheral vascular resistance, doxazosin treatment of normotensive men with BPH did not result in a clinically significant blood pressure lowering effect (Table 2). The proportion of normotensive patients with a sitting systolic blood pressure less than 90 mmHg and/or diastolic blood pressure less than 60 mmHg at any time during treatment with doxazosin 1 to 8 mg once daily was 6.7% with doxazosin and not significantly different (statistically) from that with placebo (5%).

TABLE 2 Mean Changes in Blood Pressure from Baseline to the Mean of the Final Efficacy Phase in Normotensives (Diastolic BP <90 mmHg) in Two Double-blind, Placebo-controlled U.S. Studies with doxazosin 1 to 8 mg once daily.
 | PLACEBO (N=85) |  | DOXAZOSIN (N=183)
Sitting BP (mmHg) | Baseline | Change | Baseline | Change
Systolic | 128.4 | −1.4 | 128.8 | −4.9 [p ≤0.05 compared to placebo]
Diastolic | 79.2 | −1.2 | 79.6 | −2.4
Standing BP (mmHg) | Baseline | Change | Baseline | Change
Systolic | 128.5 | −0.6 | 128.5 | −5.3
Diastolic | 80.5 | −0.7 | 80.4 | −2.6

B. Hypertension

The mechanism of action of doxazosin is selective blockade of the alpha1 (postjunctional) subtype of adrenergic receptors. Studies in normal human subjects have shown that doxazosin competitively antagonized the pressor effects of phenylephrine (an alpha1 agonist) and the systolic pressor effect of norepinephrine. Doxazosin and prazosin have similar abilities to antagonize phenylephrine. The antihypertensive effect of doxazosin results from a decrease in systemic vascular resistance. The parent compound doxazosin is primarily responsible for the antihypertensive activity. The low plasma concentrations of known active and inactive metabolites of doxazosin (2-piperazinyl, 6'- and 7'-hydroxy and 6- and 7-O-desmethyl compounds) compared to parent drug indicate that the contribution of even the most potent compound (6'-hydroxy) to the antihypertensive effect of doxazosin in man is probably small. The 6'- and 7'-hydroxy metabolites have demonstrated antioxidant properties at concentrations of 5 µM, in vitro.

Administration of doxazosin results in a reduction in systemic vascular resistance. In patients with hypertension, there is little change in cardiac output. Maximum reductions in blood pressure usually occur 2 to 6 hours after dosing and are associated with a small increase in standing heart rate. Like other alpha1-adrenergic blocking agents, doxazosin has a greater effect on blood pressure and heart rate in the standing position.

In a pooled analysis of placebo-controlled hypertension studies with about 300 hypertensive patients per treatment group, doxazosin, at doses of 1 to 16 mg given once daily, lowered blood pressure at 24 hours by about 10/8 mmHg compared to placebo in the standing position and about 9/5 mmHg in the supine position. Peak blood pressure effects (1 to 6 hours) were larger by about 50 to 75% (i.e., trough values were about 55 to 70% of peak effect), with the larger peak-trough differences seen in systolic pressures. There was no apparent difference in the blood pressure response of Caucasians and blacks or of patients above and below age 65. In these predominantly normocholesterolemic patients, doxazosin produced small reductions in total serum cholesterol (2 to 3%), LDL cholesterol (4%), and a similarly small increase in HDL/total cholesterol ratio (4%). The clinical significance of these findings is uncertain. In the same patient population, patients receiving doxazosin gained a mean of 0.6 kg compared to a mean loss of 0.1 kg for placebo patients.

Pharmacokinetics

After oral administration of therapeutic doses, peak plasma levels of doxazosin occur at about 2 to 3 hours. Bioavailability is approximately 65%, reflecting first-pass metabolism of doxazosin by the liver. The effect of food on the pharmacokinetics of doxazosin was examined in a crossover study with twelve hypertensive subjects. Reductions of 18% in mean maximum plasma concentration and 12% in the area under the concentration-time curve occurred when doxazosin was administered with food. Neither of these differences was statistically or clinically significant.

Doxazosin is extensively metabolized in the liver, mainly by O-demethylation of the quinazoline nucleus or hydroxylation of the benzodioxan moiety. Although several active metabolites of doxazosin have been identified, the pharmacokinetics of these metabolites have not been characterized. In a study of two subjects administered radiolabelled doxazosin 2 mg orally and 1 mg intravenously on two separate occasions, approximately 63% of the dose was eliminated in the feces and 9% of the dose was found in the urine. On average only 4.8% of the dose was excreted as unchanged drug in the feces and only a trace of the total radioactivity in the urine was attributed to unchanged drug. At the plasma concentrations achieved by therapeutic doses, approximately 98% of the circulating drug is bound to plasma proteins.

Plasma elimination of doxazosin is biphasic, with a terminal elimination half-life of about 22 hours. Steady-state studies in hypertensive patients given doxazosin doses of 2 to 16 mg once daily showed linear kinetics and dose proportionality. In two studies, following the administration of 2 mg orally once daily, the mean accumulation ratios (steady-state AUC vs. first-dose AUC) were 1.2 and 1.7. Enterohepatic recycling is suggested by secondary peaking of plasma doxazosin concentrations.

In a crossover study in 24 normotensive subjects, the pharmacokinetics and safety of doxazosin were shown to be similar with morning and evening dosing regimens. The area under the curve after morning dosing was, however, 11% less than that after evening dosing and the time to peak concentration after evening dosing occurred significantly later than that after morning dosing (5.6 hr vs. 3.5 hr).

The pharmacokinetics of doxazosin in young (<65 years) and elderly (≥65 years) subjects were similar for plasma half-life values and oral clearance. Pharmacokinetic studies in elderly patients and patients with renal impairment have shown no significant alterations compared to younger patients with normal renal function. Administration of a single 2 mg dose to patients with cirrhosis (Child-Pugh Class A) showed a 40% increase in exposure to doxazosin. There are only limited data on the effects of drugs known to influence the hepatic metabolism of doxazosin [e.g., cimetidine (see PRECAUTIONS, Drug Interactions)]. As with any drug wholly metabolized by the liver, use of doxazosin in patients with altered liver function should be undertaken with caution.

In two placebo-controlled studies of normotensive and hypertensive BPH patients, in which doxazosin was administered in the morning and the titration interval was two weeks and one week, respectively, trough plasma concentrations of doxazosin were similar in the two populations. Linear kinetics and dose proportionality were observed.

INDICATIONS AND USAGE

A. Benign Prostatic Hyperplasia (BPH)

Doxazosin tablets USP are indicated for the treatment of both the urinary outflow obstruction and obstructive and irritative symptoms associated with BPH: obstructive symptoms (hesitation, intermittency, dribbling, weak urinary stream, incomplete emptying of the bladder) and irritative symptoms (nocturia, daytime frequency, urgency, burning). Doxazosin tablets USP may be used in all BPH patients whether hypertensive or normotensive. In patients with hypertension and BPH, both conditions were effectively treated with doxazosin tablets USP monotherapy. Doxazosin tablets USP provide rapid improvement in symptoms and urinary flow rate in 66 to 71% of patients. Sustained improvements with doxazosin tablets USP were seen in patients treated for up to 14 weeks in double-blind studies and up to 2 years in open-label studies.

B. Hypertension

Doxazosin tablets USP are indicated for the treatment of hypertension, to lower blood pressure. Lowering blood pressure reduces the risk of fatal and nonfatal cardiovascular events, primarily strokes and myocardial infarctions. These benefits have been seen in controlled trials of antihypertensive drugs from a wide variety of pharmacologic classes, including this drug.

Control of high blood pressure should be part of comprehensive cardiovascular risk management, including, as appropriate, lipid control, diabetes management, antithrombotic therapy, smoking cessation, exercise, and limited sodium intake. Many patients will require more than one drug to achieve blood pressure goals. For specific advice on goals and management, see published guidelines, such as those of the National High Blood Pressure Education Program’s Joint National Committee on Prevention, Detection, Evaluation, and Treatment of High Blood Pressure (JNC).

Numerous antihypertensive drugs, from a variety of pharmacologic classes and with different mechanisms of action, have been shown in randomized controlled trials to reduce cardiovascular morbidity and mortality, and it can be concluded that it is blood pressure reduction, and not some other pharmacologic property of the drugs, that is largely responsible for those benefits. The largest and most consistent cardiovascular outcome benefit has been a reduction in the risk of stroke, but reductions in myocardial infarction and cardiovascular mortality also have been seen regularly.

Elevated systolic or diastolic pressure causes increased cardiovascular risk, and the absolute risk increase per mmHg is greater at higher blood pressures, so that even modest reductions of severe hypertension can provide substantial benefit. Relative risk reduction from blood pressure reduction is similar across populations with varying absolute risk, so the absolute benefit is greater in patients who are at higher risk independent of their hypertension (for example, patients with diabetes or hyperlipidemia), and such patients would be expected to benefit from more aggressive treatment to a lower blood pressure goal.

Some antihypertensive drugs have smaller blood pressure effects (as monotherapy) in black patients, and many antihypertensive drugs have additional approved indications and effects (e.g., on angina, heart failure, or diabetic kidney disease). These considerations may guide selection of therapy.

Doxazosin tablets USP may be used alone or in combination with diuretics, beta-adrenergic blocking agents, calcium channel blockers, or angiotensin-converting enzyme inhibitors.

CONTRAINDICATIONS

Doxazosin tablets are contraindicated in patients with a known sensitivity to quinazolines (e.g., prazosin, terazosin), doxazosin, or any of the inert ingredients.

WARNINGS

Syncope and "First-dose" Effect

Doxazosin, like other alpha-adrenergic blocking agents, can cause marked hypotension, especially in the upright position, with syncope and other postural symptoms such as dizziness. Marked orthostatic effects are most common with the first dose but can also occur when there is a dosage increase, or if therapy is interrupted for more than a few days. To decrease the likelihood of excessive hypotension and syncope, it is essential that treatment be initiated with the 1 mg dose. The 2, 4, and 8 mg tablets are not for initial therapy. Dosage should then be adjusted slowly (see DOSAGE AND ADMINISTRATION), with evaluations and increases in dose every two weeks to the recommended dose. Additional antihypertensive agents should be added with caution.

Patients being titrated with doxazosin should be cautioned to avoid situations where injury could result should syncope occur, during both the day and night.

In an early investigational study of the safety and tolerance of increasing daily doses of doxazosin in normotensives beginning at 1 mg/day, only 2 of 6 subjects could tolerate more than 2 mg/day without experiencing symptomatic postural hypotension. In another study of 24 healthy normotensive male subjects receiving initial doses of 2 mg/day of doxazosin, seven (29%) of the subjects experienced symptomatic postural hypotension between 0.5 and 6 hours after the first dose, necessitating termination of the study. In this study, 2 of the normotensive subjects experienced syncope. Subsequent trials in hypertensive patients always began doxazosin dosing at 1 mg/day, resulting in a 4% incidence of postural side effects at 1 mg/day with no cases of syncope.

In multiple-dose clinical trials in hypertension involving over 1500 hypertensive patients with dose titration every one to two weeks, syncope was reported in 0.7% of patients. None of these events occurred at the starting dose of 1 mg, and 1.2% (8/664) occurred at 16 mg/day.

In placebo-controlled clinical trials in BPH, 3 out of 665 patients (0.5%) taking doxazosin reported syncope. Two of the patients were taking 1 mg doxazosin, while one patient was taking 2 mg doxazosin when syncope occurred. In the open-label, long-term extension follow-up of approximately 450 BPH patients, there were 3 reports of syncope (0.7%). One patient was taking 2 mg, one patient was taking 8 mg, and one patient was taking 12 mg when syncope occurred. In a clinical pharmacology study, one subject receiving 2 mg experienced syncope.

If syncope occurs, the patient should be placed in a recumbent position and treated supportively as necessary.

Priapism

Rarely (probably less frequently than once in every several thousand patients), alpha1 antagonists, including doxazosin, have been associated with priapism (painful penile erection, sustained for hours and unrelieved by sexual intercourse or masturbation). Because this condition can lead to permanent impotence if not promptly treated, patients must be advised about the seriousness of the condition (see PRECAUTIONS, Information for Patients).

PRECAUTIONS

General

Prostate Cancer

Carcinoma of the prostate causes many of the symptoms associated with BPH and the two disorders frequently co-exist. Carcinoma of the prostate should therefore be ruled out prior to commencing therapy with doxazosin .

Cataract Surgery

Intraoperative Floppy Iris Syndrome (IFIS) has been observed during cataract surgery in some patients on or previously treated with alpha1 blockers. This variant of small pupil syndrome is characterized by the combination of a flaccid iris that billows in response to intraoperative irrigation currents, progressive intraoperative miosis despite preoperative dilation with standard mydriatic drugs, and potential prolapse of the iris toward the phacoemulsification incisions. The patient's surgeon should be prepared for possible modifications to their surgical technique, such as the utilization of iris hooks, iris dilator rings, or viscoelastic substances. There does not appear to be a benefit of stopping alpha1 blocker therapy prior to cataract surgery.

Orthostatic Hypotension

While syncope is the most severe orthostatic effect of doxazosin, other symptoms of lowered blood pressure, such as dizziness, lightheadedness, or vertigo can occur, especially at initiation of therapy or at the time of dose increases.

a) Hypertension

These symptoms were common in clinical trials in hypertension, occurring in up to 23% of all patients treated and causing discontinuation of therapy in about 2%.

In placebo-controlled titration trials in hypertension, orthostatic effects were minimized by beginning therapy at 1 mg per day and titrating every two weeks to 2, 4, or 8 mg per day. There was an increased frequency of orthostatic effects in patients given 8 mg or more, 10%, compared to 5% at 1 to 4 mg and 3% in the placebo group.

b) Benign Prostatic Hyperplasia

In placebo-controlled trials in BPH, the incidence of orthostatic hypotension with doxazosin was 0.3% and did not increase with increasing dosage (to 8 mg/day). The incidence of discontinuations due to hypotensive or orthostatic symptoms was 3.3% with doxazosin and 1% with placebo. The titration interval in these studies was one to two weeks.

Patients in occupations in which orthostatic hypotension could be dangerous should be treated with particular caution. As alpha1 antagonists can cause orthostatic effects, it is important to evaluate standing blood pressure two minutes after standing, and patients should be advised to exercise care when arising from a supine or sitting position.

If hypotension occurs, the patient should be placed in the supine position and, if this measure is inadequate, volume expansion with intravenous fluids or vasopressor therapy may be used. A transient hypotensive response is not a contraindication to further doses of doxazosin.

Information for Patients

(See patient package insert)

Patients should be made aware of the possibility of syncopal and orthostatic symptoms, especially at the initiation of therapy, and urged to avoid driving or hazardous tasks for 24 hours after the first dose, after a dosage increase, and after interruption of therapy when treatment is resumed. They should be cautioned to avoid situations where injury could result should syncope occur during initiation of doxazosin therapy. They should also be advised of the need to sit or lie down when symptoms of lowered blood pressure occur, although these symptoms are not always orthostatic, and to be careful when rising from a sitting or lying position. If dizziness, lightheadedness, or palpitations are bothersome, they should be reported to the physician, so that dose adjustment can be considered. Patients should also be told that drowsiness or somnolence can occur with doxazosin or any selective alpha1 adrenoceptor antagonist, requiring caution in people who must drive or operate heavy machinery.

Patients should be advised about the possibility of priapism as a result of treatment with alpha1 antagonists. Patients should know that this adverse event is very rare. If they experience priapism, it should be brought to immediate medical attention, for, if not treated promptly, it can lead to permanent erectile dysfunction (impotence).

Drug/Laboratory Test Interactions

Doxazosin does not affect the plasma concentration of prostate-specific antigen in patients treated for up to 3 years. Both doxazosin, an alpha1 inhibitor, and finasteride, a 5-alpha reductase inhibitor, are highly protein-bound and hepatically metabolized. There is no definitive controlled clinical experience on the concomitant use of alpha1 inhibitors and 5-alpha reductase inhibitors at this time.

Impaired Liver Function

Doxazosin should be administered with caution to patients with evidence of impaired hepatic function, or to patients receiving drugs known to influence hepatic metabolism (see CLINICAL PHARMACOLOGY, Pharmacokinetics).

Leukopenia/Neutropenia

Analysis of hematologic data from hypertensive patients receiving doxazosin in controlled hypertension clinical trials showed that the mean WBC (N=474) and mean neutrophil counts (N=419) were decreased by 2.4% and 1.0%, respectively, compared to placebo, a phenomenon seen with other alpha-blocking drugs. In BPH patients, the incidence of clinically significant WBC abnormalities was 0.4% (2/459) with doxazosin and 0% (0/147) with placebo, with no statistically significant difference between the two treatment groups. A search through a data base of 2400 hypertensive patients and 665 BPH patients revealed 4 hypertensives in which drug-related neutropenia could not be ruled out and one BPH patient in which drug-related leukopenia could not be ruled out. Two hypertensives had a single low value on the last day of treatment. Two hypertensives had stable, non-progressive neutrophil counts in the 1000/mm^3 range over periods of 20 and 40 weeks. One BPH patient had a decrease from a WBC count of 4800/mm^3 to 2700/mm^3 at the end of the study; there was no evidence of clinical impairment. In cases where follow-up was available, the WBCs and neutrophil counts returned to normal after discontinuation of doxazosin. No patients became symptomatic as a result of the low WBC or neutrophil counts.

Drug Interactions

Most (98%) of plasma doxazosin is protein bound. In vitro data in human plasma indicate that doxazosin has no effect on protein binding of digoxin, warfarin, phenytoin, or indomethacin. There is no information on the effect of other highly plasma protein- bound drugs on doxazosin binding. Doxazosin has been administered without any evidence of an adverse drug interaction to patients receiving thiazide diuretics, beta-blocking agents, and nonsteroidal anti-inflammatory drugs. In a placebo-controlled trial in normal volunteers, the administration of a single 1 mg dose of doxazosin on day 1 of a four-day regimen of oral cimetidine (400 mg twice daily) resulted in a 10% increase in mean AUC of doxazosin (p=0.006), and a slight but not statistically significant increase in mean Cmax and mean half-life of doxazosin. The clinical significance of this increase in doxazosin AUC is unknown.

In clinical trials, doxazosin tablets have been administered to patients on a variety of concomitant medications; while no formal interaction studies have been conducted, no interactions were observed. Doxazosin tablets have been used with the following drugs or drug classes: 1) analgesic/anti-inflammatory (e.g., acetaminophen, aspirin, codeine and codeine combinations, ibuprofen, indomethacin); 2) antibiotics (e.g., erythromycin, trimethoprim and sulfamethoxazole, amoxicillin); 3) antihistamines (e.g., chlorpheniramine); 4) cardiovascular agents (e.g., atenolol, hydrochlorothiazide, propranolol); 5) corticosteroids; 6) gastrointestinal agents (e.g., antacids); 7) hypoglycemics and endocrine drugs; 8) sedatives and tranquilizers (e.g., diazepam); 9) cold and flu remedies.

Concomitant administration of doxazosin with a phosphodiesterase-5 (PDE-5) inhibitor can result in additive blood pressure lowering effects and symptomatic hypotension (see DOSAGE AND ADMINISTRATION).

Cardiac Toxicity in Animals

An increased incidence of myocardial necrosis or fibrosis was displayed by Sprague-Dawley rats after 6 months of dietary administration at concentrations calculated to provide 80 mg doxazosin/kg/day, and after 12 months of dietary administration at concentrations calculated to provide 40 mg doxazosin/kg/day (AUC exposure in rats 8 times the human AUC exposure with a 12 mg/day therapeutic dose). Myocardial fibrosis was observed in both rats and mice treated in the same manner with 40 mg doxazosin/kg/day for 18 months (exposure 8 times human AUC exposure in rats and somewhat equivalent to human Cmax exposure in mice). No cardiotoxicity was observed at lower doses (up to 10 or 20 mg/kg/day, depending on the study) in either species. These lesions were not observed after 12 months of oral dosing in dogs at maximum doses of 20 mg/kg/day [maximum plasma concentrations (Cmax) in dogs 14 times the Cmax exposure in humans receiving a 12 mg/day therapeutic dose] and in Wistar rats at doses of 100 mg/kg/day (Cmax exposures 15 times human Cmax exposure with a 12 mg/day therapeutic dose). There is no evidence that similar lesions occur in humans.

Carcinogenesis, Mutagenesis, Impairment of Fertility

Chronic dietary administration (up to 24 months) of doxazosin mesylate at maximally tolerated doses of 40 mg/kg/day in rats and 120 mg/kg/day in mice revealed no evidence of carcinogenic potential. The highest doses evaluated in the rat and mouse studies are associated with AUCs (a measure of systemic exposure) that are 8 times and 4 times, respectively, the human AUC at a dose of 16 mg/day.

Mutagenicity studies revealed no drug- or metabolite-related effects at either chromosomal or subchromosomal levels.

Studies in rats showed reduced fertility in males treated with doxazosin at oral doses of 20 (but not 5 or 10) mg/kg/day, about 4 times the AUC exposures obtained with a 12 mg/day human dose. This effect was reversible within two weeks of drug withdrawal. There have been no reports of any effects of doxazosin on male fertility in humans.

Pregnancy

Teratogenic Effects, Pregnancy Category C

Studies in pregnant rabbits and rats at daily oral doses of up to 41 and 20 mg/kg, respectively (plasma drug concentrations 10 and 4 times human Cmax and AUC exposures with a 12 mg/day therapeutic dose), have revealed no evidence of harm to the fetus. A dosage regimen of 82 mg/kg/day in the rabbit was associated with reduced fetal survival. There are no adequate and well-controlled studies in pregnant women. Because animal reproduction studies are not always predictive of human response, doxazosin should be used during pregnancy only if clearly needed.

Radioactivity was found to cross the placenta following oral administration of labelled doxazosin to pregnant rats.

Nonteratogenic Effects

In peri-postnatal studies in rats, postnatal development at maternal doses of 40 or 50 mg/kg/day of doxazosin (8 times human AUC exposure with a 12 mg/day therapeutic dose) was delayed, as evidenced by slower body weight gain and slightly later appearance of anatomical features and reflexes.

Nursing Mothers

Studies in lactating rats given a single oral dose of 1 mg/kg of [2-^14C]-doxazosin indicate that doxazosin accumulates in rat breast milk with a maximum concentration about 20 times greater than the maternal plasma concentration. It is not known whether this drug is excreted in human milk. Because many drugs are excreted in human milk, caution should be exercised when doxazosin is administered to a nursing mother.

Pediatric Use

The safety and effectiveness of doxazosin as an antihypertensive agent have not been established in children.

Geriatric Use

The safety and effectiveness profile of doxazosin in BPH was similar in the elderly (age ≥ 65 years) and younger (age < 65 years) patients.

For hypertension: Clinical studies of doxazosin did not include sufficient numbers of subjects aged 65 and over to determine whether they respond differently from younger subjects. Other reported clinical experience has not identified differences in responses between the elderly and younger patients. In general, dose selection for an elderly patient should be cautious, usually starting at the low end of the dosing range, reflecting the greater frequency of decreased hepatic, renal or cardiac function, and of concomitant disease or other drug therapy.

ADVERSE REACTIONS

A. Benign Prostatic Hyperplasia (BPH)

The incidence of adverse events has been ascertained from worldwide clinical trials in 965 BPH patients. The incidence rates presented below (Table 3) are based on combined data from seven placebo-controlled trials involving once-daily administration of doxazosin in doses of 1 to 16 mg in hypertensives and 0.5 to 8 mg in normotensives. The adverse events when the incidence in the doxazosin group was at least 1% are summarized in Table 3. No significant difference in the incidence of adverse events compared to placebo was seen except for dizziness, fatigue, hypotension, edema, and dyspnea. Dizziness and dyspnea appeared to be dose-related.

TABLE 3 ADVERSE REACTIONS DURING PLACEBO-CONTROLLED STUDIES BENIGN PROSTATIC HYPERPLASIA
 | DOXAZOSIN | PLACEBO
Body System | (N=665) | (N=300)
BODY AS A WHOLE
Back Pain | 1.8% | 2.0%
Chest Pain | 1.2% | 0.7%
Fatigue | 8.0% [p ≤0.05 for treatment differences] | 1.7%
Headache | 9.9% | 9.0%
Influenza-like Symptoms | 1.1% | 1.0%
Pain | 2.0% | 1.0%
CARDIOVASCULAR SYSTEM
Hypotension | 1.7% | 0.0%
Palpitation | 1.2% | 0.3%
DIGESTIVE SYSTEM
Abdominal Pain | 2.4% | 2.0%
Diarrhea | 2.3% | 2.0%
Dyspepsia | 1.7% | 1.7%
Nausea | 1.5% | 0.7%
METABOLIC AND NUTRITIONAL DISORDERS
Edema | 2.7% | 0.7%
NERVOUS SYSTEM
Dizziness [Includes vertigo] | 15.6% | 9.0%
Mouth Dry | 1.4% | 0.3%
Somnolence | 3.0% | 1.0%
RESPIRATORY SYSTEM
Dyspnea | 2.6% | 0.3%
Respiratory Disorder | 1.1% | 0.7%
SPECIAL SENSES
Vision Abnormal | 1.4% | 0.7%
UROGENITAL SYSTEM
Impotence | 1.1% | 1.0%
Urinary Tract Infection | 1.4% | 2.3%
SKIN & APPENDAGES
Sweating Increased | 1.1% | 1.0%
PSYCHIATRIC DISORDERS
Anxiety | 1.1% | 0.3%
Insomnia | 1.2% | 0.3%

In these placebo-controlled studies of 665 doxazosin patients treated for a mean of 85 days, additional adverse reactions have been reported. These are less than 1% and not distinguishable from those that occurred in the placebo group. Adverse reactions with an incidence of less than 1% but of clinical interest are (doxazosin vs. placebo): Cardiovascular System: angina pectoris (0.6% vs. 0.7%), postural hypotension (0.3% vs. 0.3%), syncope (0.5% vs. 0.0%), tachycardia (0.9% vs. 0.0%); Urogenital System: dysuria (0.5% vs. 1.3%); and Psychiatric Disorders: libido decreased (0.8% vs. 0.3%). The safety profile in patients treated for up to three years was similar to that in the placebo-controlled studies.

The majority of adverse experiences with doxazosin were mild.

B. Hypertension

Doxazosin has been administered to approximately 4000 hypertensive patients, of whom 1679 were included in the hypertension clinical development program. In that program, minor adverse effects were frequent, but led to discontinuation of treatment in only 7% of patients. In placebo-controlled studies, adverse effects occurred in 49% and 40% of patients in the doxazosin and placebo groups, respectively, and led to discontinuation in 2% of patients in each group. The major reasons for discontinuation were postural effects (2%), edema, malaise/fatigue, and some heart rate disturbance, each about 0.7%.

In controlled hypertension clinical trials directly comparing doxazosin to placebo, there was no significant difference in the incidence of side effects, except for dizziness (including postural), weight gain, somnolence, and fatigue/malaise. Postural effects and edema appeared to be dose-related. The prevalence rates presented below are based on combined data from placebo-controlled studies involving once-daily administration of doxazosin at doses ranging from 1 to 16 mg. Table 4 summarizes those adverse experiences (possibly/probably related) reported for patients in these hypertension studies where the prevalence rate in the doxazosin group was at least 0.5% or where the reaction is of particular interest.

TABLE 4 ADVERSE REACTIONS DURING PLACEBO-CONTROLLED STUDIES
 | HYPERTENSION
 | DOXAZOSIN | PLACEBO
 | (N=339) | (N=336)
CARDIOVASCULAR SYSTEM
Dizziness | 19% | 9%
Vertigo | 2% | 1%
Postural Hypotension | 0.3% | 0%
Edema | 4% | 3%
Palpitation | 2% | 3%
Arrhythmia | 1% | 0%
Hypotension | 1% | 0%
Tachycardia | 0.3% | 1%
Peripheral Ischemia | 0.3% | 0%
SKIN & APPENDAGES
Rash | 1% | 1%
Pruritus | 1% | 1%
MUSCULOSKELETAL SYSTEM
Arthralgia/Arthritis | 1% | 0%
Muscle Weakness | 1% | 0%
Myalgia | 1% | 0%
CENTRAL & PERIPHERAL N.S.
Headache | 14% | 16%
Paresthesia | 1% | 1%
Kinetic Disorders | 1% | 0%
Ataxia | 1% | 0%
Hypertonia | 1% | 0%
Muscle Cramps | 1% | 0%
AUTONOMIC
Mouth Dry | 2% | 2%
Flushing | 1% | 0%
SPECIAL SENSES
Vision Abnormal | 2% | 1%
Conjunctivitis/Eye Pain | 1% | 1%
Tinnitus | 1% | 0.3%
PSYCHIATRIC
Somnolence | 5% | 1%
Nervousness | 2% | 2%
Depression | 1% | 1%
Insomnia | 1% | 1%
Sexual Dysfunction | 2% | 1%
GASTROINTESTINAL
Nausea | 3% | 4%
Diarrhea | 2% | 3%
Constipation | 1% | 1%
Dyspepsia | 1% | 1%
Flatulence | 1% | 1%
Abdominal Pain | 0% | 2%
Vomiting | 0% | 1%
RESPIRATORY
Rhinitis | 3% | 1%
Dyspnea | 1% | 1%
Epistaxis | 1% | 0%
URINARY
Polyuria | 2% | 0%
Urinary Incontinence | 1% | 0%
Micturition Frequency | 0% | 2%
GENERAL
Fatigue/Malaise | 12% | 6%
Chest Pain | 2% | 2%
Asthenia | 1% | 1%
Face Edema | 1% | 0%
Pain | 2% | 2%

Additional adverse reactions have been reported, but these are, in general, not distinguishable from symptoms that might have occurred in the absence of exposure to doxazosin. The following adverse reactions occurred with a frequency of between 0.5% and 1%: syncope, hypoesthesia, increased sweating, agitation, increased weight. The following additional adverse reactions were reported by <0.5% of 3960 patients who received doxazosin in controlled or open, short- or long-term clinical studies, including international studies. Cardiovascular System: angina pectoris, myocardial infarction, cerebrovascular accident; Autonomic Nervous System: pallor; Metabolic: thirst, gout, hypokalemia; Hematopoietic: lymphadenopathy, purpura; Reproductive System: breast pain; Skin Disorders: alopecia, dry skin, eczema; Central Nervous System: paresis, tremor, twitching, confusion, migraine, impaired concentration; Psychiatric: paroniria, amnesia, emotional lability, abnormal thinking, depersonalization; Special Senses: parosmia, earache, taste perversion, photophobia, abnormal lacrimation; Gastrointestinal System: increased appetite, anorexia, fecal incontinence, gastroenteritis; Respiratory System: bronchospasm, sinusitis, coughing, pharyngitis; Urinary System: renal calculus; General Body System: hot flushes, back pain, infection, fever/rigors, decreased weight, influenza-like symptoms.

Doxazosin has not been associated with any clinically significant changes in routine biochemical tests. No clinically relevant adverse effects were noted on serum potassium, serum glucose, uric acid, blood urea nitrogen, creatinine or liver function tests. Doxazosin has been associated with decreases in white blood cell counts (see PRECAUTIONS, Leukopenia/Neutropenia).

In post-marketing experience, the following additional adverse reactions have been reported: Autonomic Nervous System: priapism; Central Nervous System: hypoesthesia; Endocrine System: gynecomastia; Gastrointestinal System: vomiting; General Body System: allergic reaction; Heart Rate/Rhythm: bradycardia; Hematopoietic: leukopenia, thrombocytopenia; Liver/Biliary System: hepatitis, hepatitis cholestatic; Respiratory System: bronchospasm aggravated; Skin Disorders: urticaria; Special Senses: Intraoperative Floppy Iris Syndrome (see PRECAUTIONS, Cataract Surgery); Urinary System: hematuria, micturition disorder, micturition frequency, nocturia.

OVERDOSAGE

Experience with doxazosin overdosage is limited. Two adolescents, who each intentionally ingested 40 mg doxazosin with diclofenac or acetaminophen, were treated with gastric lavage with activated charcoal and made full recoveries. A two-year-old child who accidently ingested 4 mg doxazosin was treated with gastric lavage and remained normotensive during the five-hour emergency room observation period. A six-month-old child accidentally received a crushed 1 mg tablet of doxazosin and was reported to have been drowsy. A 32-year-old female with chronic renal failure, epilepsy, and depression intentionally ingested 60 mg doxazosin (blood level = 0.9 µg/mL; normal values in hypertensives = 0.02 µg/mL); death was attributed to a grand mal seizure resulting from hypotension. A 39-year-old female who ingested 70 mg doxazosin, alcohol, and Dalmane® (flurazepam) developed hypotension which responded to fluid therapy.

The oral LD50 of doxazosin is greater than 1000 mg/kg in mice and rats. The most likely manifestation of overdosage would be hypotension, for which the usual treatment would be intravenous infusion of fluid. As doxazosin is highly protein bound, dialysis would not be indicated.

DOSAGE AND ADMINISTRATION

DOSAGE MUST BE INDIVIDUALIZED. The initial dosage of doxazosin tablets in patients with hypertension and/or BPH is 1 mg given once daily in the a.m. or p.m. This starting dose is intended to minimize the frequency of postural hypotension and first-dose syncope associated with doxazosin tablets. Postural effects are most likely to occur between 2 and 6 hours after a dose. Therefore, blood pressure measurements should be taken during this time period after the first dose and with each increase in dose. If doxazosin tablets administration is discontinued for several days, therapy should be restarted using the initial dosing regimen.

Concomitant administration of doxazosin tablets with a PDE-5 inhibitor can result in additive blood pressure lowering effects and symptomatic hypotension; therefore, PDE-5 inhibitor therapy should be initiated at the lowest dose in patients taking doxazosin tablets.

A. BENIGN PROSTATIC HYPERPLASIA 1 to 8 mg once daily

The initial dosage of doxazosin tablet is 1 mg, given once daily in the a.m. or p.m. Depending on the individual patient's urodynamics and BPH symptomatology, dosage may then be increased to 2 mg and thereafter to 4 mg and 8 mg once daily, the maximum recommended dose for BPH. The recommended titration interval is 1 to 2 weeks. Blood pressure should be evaluated routinely in these patients.

B. HYPERTENSION 1 to 16 mg once daily

The initial dosage of doxazosin tablet is 1 mg given once daily. Depending on the individual patient's standing blood pressure response (based on measurements taken at 2 to 6 hours post-dose and 24 hours post-dose), dosage may then be increased to 2 mg and thereafter if necessary to 4 mg, 8 mg and 16 mg to achieve the desired reduction in blood pressure. Increases in dose beyond 4 mg increase the likelihood of excessive postural effects, including syncope, postural dizziness/vertigo and postural hypotension. At a titrated dose of 16 mg once daily, the frequency of postural effects is about 12% compared to 3% for placebo.

HOW SUPPLIED

4 mg: Cream to yellow coloured, round, biconvex uncoated tablets, debossed with “C4” on one side and breakline on other side, may have mottled appearance and supplied as follows:

NDC 66267-377-90 Bottle of 90

NDC 66267-377-30 Bottle of 30

Recommended Storage: Store at 20° to 25°C (68° to 77°F); excursions permitted to 15° to 30°C (59° to 86°F) [see USP Controlled Room Temperature].

Manufactured For:
Accord Healthcare, Inc.,
1009 Slater Road,
Suite 210-B,
Durham, NC 27703,
USA

Manufactured By:
Intas Pharmaceuticals Limited.
Plot No. : 457, 458,
Village Matoda,
Bavla Road, Ta.- Sanand,
Dist. Ahmedabad-382 210,
INDIA

10 10514 0 627955
Issued December 2013

PATIENT INFORMATION ABOUT Doxazosin Tablets USP FOR BENIGN PROSTATIC HYPERPLASIA (BPH)

Read this leaflet:

- before you start taking doxazosin tablets
- each time you get a new prescription.

You and your doctor should discuss this treatment and your BPH symptoms before you start taking doxazosin tablets and at your regular checkups. This leaflet does NOT take the place of discussions with your doctor.

Doxazosin tablets are used to treat both benign prostatic hyperplasia (BPH) and high blood pressure (hypertension). This leaflet describes doxazosin tablets as treatment for BPH (although you may be taking doxazosin tablets for both your BPH and high blood pressure).

What is BPH?

BPH is an enlargement of the prostate gland. This gland surrounds the tube that drains the urine from the bladder. The symptoms of BPH can be caused by a tensing of the enlarged muscle in the prostate gland which blocks the passage of urine. This can lead to such symptoms as:

- a weak or start-and-stop stream when urinating
- a feeling that the bladder is not completely emptied after urination
- a delay or difficulty in the beginning of urination
- a need to urinate often during the day and especially at night
- a feeling that you must urinate immediately

Treatment Options for BPH

The four main treatment options for BPH are:

- If you are not bothered by your symptoms, you and your doctor may decide on a program of "watchful waiting." It is not an active treatment like taking medication or surgery but involves having regular checkups to see if your condition is getting worse or causing problems.
- Treatment with doxazosin tablets or other similar drugs. Doxazosin tablets are the medication your doctor has prescribed for you. See "What Doxazosin Tablets Does," below.
- Treatment with the medication class of 5-alpha reductase inhibitors (e.g., Proscar®). It can cause the prostate to shrink. It may take 6 months or more for the full benefit of finasteride to be seen.
- Various surgical procedures. Your doctor can describe these procedures to you. The best procedure for you depends on your BPH symptoms and medical condition.

What Doxazosin Tablets Does

Doxazosin tablets works on a specific type of muscle found in the prostate, causing it to relax. This in turn decreases the pressure within the prostate, thus improving the flow of urine and your symptoms.

- Doxazosin tablets help relieve the symptoms of BPH (weak stream, start-and-stop stream, a feeling that your bladder is not completely empty, delay in beginning of urination, need to urinate often during the day and especially at night, and feeling that you must urinate immediately). It does not change the size of the prostate. The prostate may continue to grow; however, a larger prostate is not necessarily related to more symptoms or to worse symptoms. Doxazosin tablets can decrease your symptoms and improve urinary flow, without decreasing the size of the prostate.
- If doxazosin tablets are helping you, you should notice an effect within 1 to 2 weeks after you start your medication. Doxazosin tablets have been studied in over 900 patients for up to 2 years and the drug has been shown to continue to work during long-term treatment. Even though you take doxazosin tablets and it may help you, doxazosin tablets may not prevent the need for surgery in the future.
- Doxazosin tablet does not affect PSA levels. PSA is the abbreviation for Prostate Specific Antigen. Your doctor may have done a blood test called PSA. You may want to ask your doctor more about this if you have had a PSA test done.

Other Important Facts

- You should see an improvement of your symptoms within 1 to 2 weeks. In addition to your other regular checkups you will need to continue seeing your doctor regularly to check your progress regarding your BPH and to monitor your blood pressure.
- Doxazosin tablets are not a treatment for prostate cancer. Your doctor has prescribed doxazosin tablets for your BPH and not for prostate cancer; however, a man can have BPH and prostate cancer at the same time. Doctors usually recommend that men be checked for prostate cancer once a year when they turn 50 (or 40 if a family member has had prostate cancer). A higher incidence of prostate cancer has been noted in men of African-American descent. These checks should continue even if you are taking doxazosin tablets. .

How To Take Doxazosin Tablets and What You Should Know While Taking Doxazosin Tablets for BPH

Doxazosin Tablets Can Cause a Sudden Drop in Blood Pressure After the VERY FIRST DOSE. You may feel dizzy, faint or "light-headed," especially after you stand up from a lying or sitting position. This is more likely to occur after you've taken the first few doses or if you increase your dose, but can occur at any time while you are taking the drug. It can also occur if you stop taking the drug and then restart treatment. If you feel very dizzy, faint or "light-headed" you should contact your doctor. Your doctor will discuss with you how often you need to visit and how often your blood pressure should be checked.

Your blood pressure should be checked when you start taking doxazosin tablets even if you do not have high blood pressure (hypertension). Your doctor will discuss with you the details of how blood pressure is measured.

Blood Pressure Measurement: Whatever equipment is used, it is usual for your blood pressure to be measured in the following way: measure your blood pressure after lying quietly on your back for five minutes. Then, after standing for two minutes measure your blood pressure again. Your doctor will discuss with you what other times during the day your blood pressure should be taken, such as two to six hours after a dose, before bedtime or after waking up in the morning. Note that moderate to high-intensity exercise can, over a period of time, lower your average blood pressure.

You can take doxazosin tablets either in the morning or at bedtime and it will be equally effective. If you take doxazosin tablets at bedtime but need to get up from bed to go to the bathroom, get up slowly and cautiously until you are sure how the medication affects you. It is important to get up slowly from a chair or bed at any time until you learn how you react to doxazosin tablets. You should not drive or do any hazardous tasks until you are used to the effects of the medication. If you begin to feel dizzy, sit or lie down until you feel better.

- You will start with a 1 mg dose of doxazosin tablets once daily. Then the once daily dose will be increased as your body gets used to the effects of the medication. Follow your doctor's instructions about how to take doxazosin tablets. You must take it every day at the dose prescribed. Talk with your doctor if you don't take it for a few days for some reason; you may then need to restart the medication at a 1 mg dose, increase your dose gradually and again be cautious about possible dizziness. Do not share doxazosin tablets with anyone else; it was prescribed only for you.
- Other side effects you could have while taking doxazosin tablets, in addition to lowering of the blood pressure, include dizziness, fatigue (tiredness), swelling of the feet and shortness of breath. Most side effects are mild. However, you should discuss any unexpected effects you notice with your doctor.
- WARNING: Extremely rarely, doxazosin tablets and similar medications have caused painful erection of the penis, sustained for hours and unrelieved by sexual intercourse or masturbation. This condition is serious, and if untreated it can be followed by permanent inability to have an erection. If you have a prolonged abnormal erection, call your doctor or go to an emergency room as soon as possible.
- Tell your surgeon if you take or have taken doxazosin tablets if you plan to have surgery for cataracts (clouding of the eye). During cataract surgery, a condition called Intraoperative Floppy Iris Syndrome (IFIS) can happen if you take or have taken doxazosin tablets.
- If you use doxazosin tablets with an oral erectile dysfunction medicine (phosphodiesterase-5 (PDE-5) inhibitor), it can cause a sudden drop in your blood pressure and you can become dizzy or faint. Talk with your healthcare provider before using PDE-5 inhibitors.
- Keep doxazosin tablets and all medicines out of the reach of children.

FOR MORE INFORMATION ABOUT DOXAZOSIN TABLETS AND BPH TALK WITH YOUR DOCTOR, NURSE, PHARMACIST OR OTHER HEALTH CARE PROVIDER.

Manufactured For:
Accord Healthcare, Inc.,
1009 Slater Road,
Suite 210-B,
Durham, NC 27703,
USA.

Manufactured By:
Intas Pharmaceuticals Limited,
Plot No. : 457, 458,
Village – Matoda,
Bavla Road, Ta.- Sanand,
Dist.- Ahmedabad – 382 210,
INDIA.

10 10514 0 627955

Issued December 2013